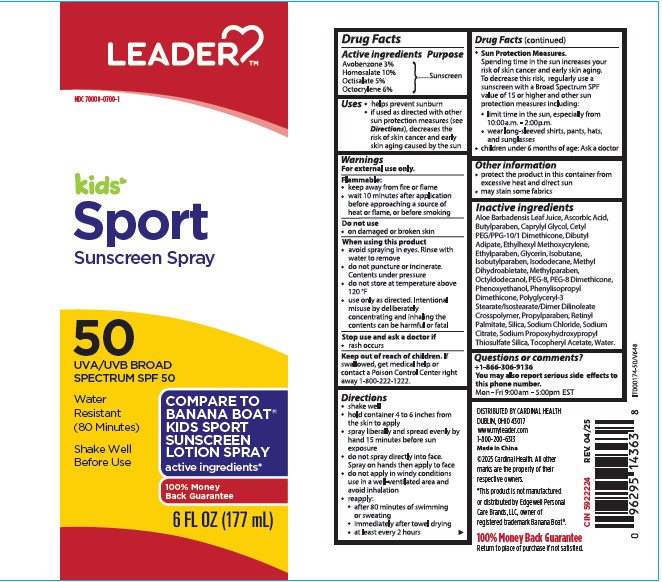 DRUG LABEL: Leader Kids Sport Sunscreen SPF 50
NDC: 70000-0700 | Form: SPRAY
Manufacturer: CARDINAL HEALTH 110, LLC. DBA LEADER
Category: otc | Type: HUMAN OTC DRUG LABEL
Date: 20250619

ACTIVE INGREDIENTS: OCTISALATE 5 g/100 mL; OCTOCRYLENE 6 g/100 mL; AVOBENZONE 3 g/100 mL; HOMOSALATE 10 g/100 mL
INACTIVE INGREDIENTS: ALOE BARBADENSIS LEAF JUICE; ASCORBIC ACID; BUTYLPARABEN; CAPRYLYL GLYCOL; CETYL PEG/PPG-10/1 DIMETHICONE (HLB 2); DIBUTYL ADIPATE; ETHYLHEXYL METHOXYCRYLENE; ETHYLPARABEN; GLYCERIN; ISOBUTANE; ISOBUTYLPARABEN; ISODODECANE; METHYL DIHYDROABIETATE; METHYLPARABEN; OCTYLDODECANOL; PEG-8; PEG-8 DIMETHICONE; PHENOXYETHANOL; PROPYLPARABEN; RETINYL PALMITATE; SILICA; SODIUM CHLORIDE; SODIUM CITRATE; SODIUM PROPOXYHYDROXYPROPYL THIOSULFATE SILICA; ALPHA-TOCOPHEROL ACETATE; WATER

Active Ingredients

Avobenzone 3.0%, Homosalate 10.0%, Octisalate 5.0%, Octocrylene 6.0%

Purpose

Sunscreen

Uses

• helps prevent sunburn • If used as directed with other sun protectiion measures (see Directions), decreases the risk of skin cancer and early skin aging caused by the sun.

Warnings

For external use only.

Flammable:

• keep away from fire or flame

• wait 10 minutes after application before approaching a source of heat or flame, or before smoking

Do not use

• on damaged or broken skin.

When using this product

• avoid spraying eyes. Rinse with water to remove

• do not puncture or incinerate. Contents under pressure.

• do not store at temperature above 120 F

• use only as directed. Intentional misure by deliberately concentrating and inhaling the contents can be harmful or fatal

Stop use and ask a doctor if

• rash occurs.

Keep out of reach of children.

If product is swallowed, get medical help or contact a Poison Control Center right away 1-800-222-1222.

Directions

• Shake well

• hold container 4 to 6 inches from the skin to apply

• spray liberally and evenly by hand 15 minutes before sun exposure

• do not spray directly into face. Spray on hands then apply to face

• do not apply in windy conditions, use in well-ventilated area and avoid inhalation

• reapply:

• after 80 minues of swimming or sweating

• immediately after towel drying

• at least every 2 hours

• Sun Protection Measures.

Spending time in the sun increases your risk of skin cancer and early skin aging. To decrease this risk, regularly use a sunscreen with a broad spectrum SPF of 15 or higher and other sun protection measures including:

• limit time in the sun, especially from 10:00 a.m.-2:00 p.m.

• wear long-sleeve shirts, pants, hats, and sunglasses

• children under 6 months of age: Ask a doctor.

Inactive ingredients

Aloe Barbadensis Leaf Juice, Ascorbic Acid,
Butylparaben, Caprylyl Glycol, Cetyl
PEG/PPG-10/1 Dimethicone, Dibutyl
Adipate, Ethylhexyl Methoxycrylene,
Ethylparaben, Glycerin, Isobutane,
Isobutylparaben, Isododecane, Methyl
Dihydroabietate, Methylparaben,
Octyldodecanol, PEG-8, PEG-8 Dimethicone,
Phenoxyethanol, Phenylisopropyl
Dimethicone, Polyglyceryl-3
Stearate/Isostearate/Dimer Dilinoleate
Crosspolymer, Propylparaben, Retinyl
Palmitate, Silica, Sodium Chloride, Sodium
Citrate, Sodium Propoxyhydroxypropyl
Thiosulfate Silica, Tocopheryl Acetate, Water.

Other Information

• protect the product in this container from excessive heat and direct sun

• may stain sime fabrics

Questions or comments?

+1-866-306-9136

You may also report serious side effects to this phone number.

Mon - Fri 9:00 am - 5:00 pm EST